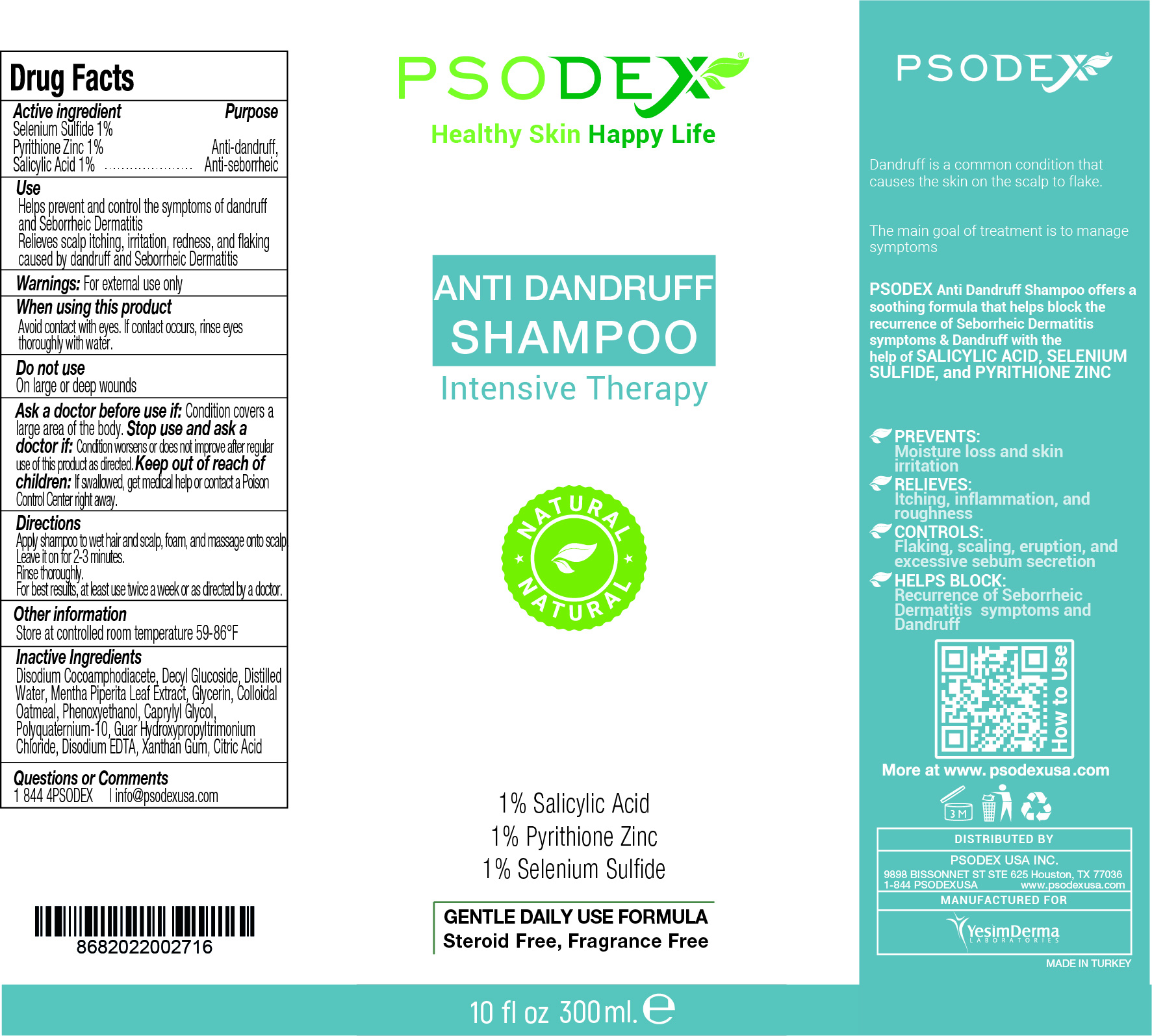 DRUG LABEL: Anti Dandruff
NDC: 73503-012 | Form: SHAMPOO
Manufacturer: PSODEX USA INC
Category: otc | Type: HUMAN OTC DRUG LABEL
Date: 20231221

ACTIVE INGREDIENTS: PYRITHIONE ZINC 1 g/100 mL; SELENIUM SULFIDE 1 g/100 mL; SALICYLIC ACID 1 g/100 mL
INACTIVE INGREDIENTS: DISODIUM COCOAMPHODIACETATE 20 g/100 mL; GLYCERIN 2 g/100 mL; PHENOXYETHANOL 0.5 g/100 mL; DECYL GLUCOSIDE 10 g/100 mL; POLYQUATERNIUM-10 (1000 MPA.S AT 2%) 0.5 g/100 mL; XANTHAN GUM 0.3 g/100 mL; EDETATE DISODIUM ANHYDROUS 0.5 g/100 mL; WATER 55.9 mL/100 mL; MENTHA PIPERITA LEAF 5 g/100 mL; OATMEAL 1 g/100 mL; CAPRYLYL GLYCOL 0.5 g/100 mL; GUAR HYDROXYPROPYLTRIMONIUM CHLORIDE (1.7 SUBSTITUENTS PER SACCHARIDE) 0.5 g/100 mL; CITRIC ACID MONOHYDRATE 0.3 g/100 mL

Anti Dandruff Shampoo Intensive Therapy

DESCRIPTION

Dandruff is a common condition that causes the skin on the scalp to flake.

The main goal of treatment is to manage symptoms

PSODEX Anti Dandruff Shampoo offers a soothing formula that helps block the recurrence of Seborrheic Dermatitis symptoms & Dandruff with the help of SALICYLIC ACID, SELENIUM SULFIDE, and PYRITHIONE ZINC

PREVENTS:
Moisture loss and skin irritation

RELIEVES:
Itching, inflammation, and roughness

CONTROLS:
Flaking, scaling, eruption, and excessive sebum secretion

HELPS BLOCK:
Recurrence of Seborrheic Dermatitis symptoms and Dandruff

Active ingredient

Selenium Sulfide 1%
Pyrithione Zinc 1%
Salicylic Acid 1%

Active ingredient

Selenium Sulfide 1%
Pyrithione Zinc 1%
Salicylic Acid 1%

Inactive Ingredients

Disodium Cocoamphodiacete, Decyl Glucoside, Distilled
Water, Mentha Piperita Leaf Extract, Glycerin, Colloidal
Oatmeal, Phenoxyethanol, Caprylyl Glycol,
Polyquaternium-10, Guar Hydroxypropyltrimonium
Chloride, Disodium EDTA, Xanthan Gum, Citric Acid

Directions

Apply shampoo to wet hair and scalp, foam, and massage onto scalp.
Leave it on for 2-3 minutes.
Rinse thoroughly.
For best results, at least use twice a week or as directed by a doctor.

Use

Helps prevent and control the symptoms of dandruff
and Seborrheic Dermatitis
Relieves scalp itching, irritation, redness, and flaking
caused by dandruff and Seborrheic Dermatitis

Purpose

Anti-dandruff,
Anti-seborrheic

Warnings:

For external use only

Other information

Store at controlled room temperature 59-86°F

Ask a doctor before use if:

Condition covers a
large area of the body.

Keep out of reach of children:

If swallowed, get medical help or contact a Poison Control Center right away.

Do not use

On large or deep wounds

Stop use and ask a doctor if:

Condition worsens or does not improve after regular use of this product as directed

Questions or Comments

1 844 4PSODEX | info@psodexusa.com

When using this product

Avoid contact with eyes. If contact occurs, rinse eyes thoroughly with water.

INFORMATION FOR OWNERS/CAREGIVERS

DISTRIBUTED BY: Psodex USA Inc.

9898 Bissonnet St Ste 625 Houston, TX 77036

1-844 4PSODEX www.psodexusa.com

MANUFACTURED FOR

Yesim Derma Laboratories